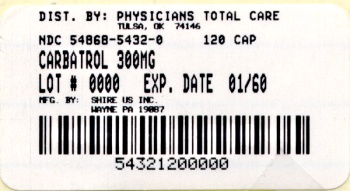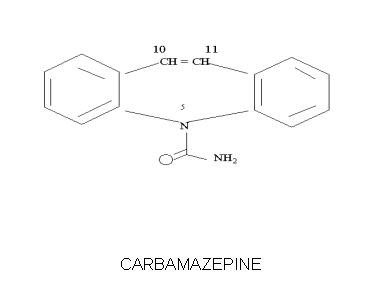 DRUG LABEL: Carbatrol
NDC: 54868-5432 | Form: CAPSULE, EXTENDED RELEASE
Manufacturer: Physicians Total Care, Inc.
Category: prescription | Type: HUMAN PRESCRIPTION DRUG LABEL
Date: 20120314

ACTIVE INGREDIENTS: CARBAMAZEPINE 300 mg/1 1
INACTIVE INGREDIENTS: CITRIC ACID MONOHYDRATE; SILICON DIOXIDE; LACTOSE MONOHYDRATE; CELLULOSE, MICROCRYSTALLINE; POLYETHYLENE GLYCOL; POVIDONE; SODIUM LAURYL SULFATE; TALC; TRIETHYL CITRATE; GELATIN; FD&C BLUE NO. 2; FD&C YELLOW NO. 6; FERRIC OXIDE RED; FERRIC OXIDE YELLOW; TITANIUM DIOXIDE

WARNING
APLASTIC ANEMIA AND AGRANULOCYTOSIS HAVE BEEN REPORTED IN ASSOCIATION WITH THE USE OF CARBAMAZEPINE. DATA FROM A POPULATION-BASED CASE-CONTROL STUDY DEMONSTRATE THAT THE RISK OF DEVELOPING THESE REACTIONS IS 5-8 TIMES GREATER THAN IN THE GENERAL POPULATION. HOWEVER, THE OVERALL RISK OF THESE REACTIONS IN THE UNTREATED GENERAL POPULATION IS LOW, APPROXIMATELY SIX PATIENTS PER ONE MILLION POPULATION PER YEAR FOR AGRANULOCYTOSIS AND TWO PATIENTS PER ONE MILLION POPULATION PER YEAR FOR APLASTIC ANEMIA.
ALTHOUGH REPORTS OF TRANSIENT OR PERSISTENT DECREASED PLATELET OR WHITE BLOOD CELL COUNTS ARE NOT UNCOMMON IN ASSOCIATION WITH THE USE OF CARBAMAZEPINE, DATA ARE NOT AVAILABLE TO ESTIMATE ACCURATELY THEIR INCIDENCE OR OUTCOME. HOWEVER, THE VAST MAJORITY OF THE CASES OF LEUKOPENIA HAVE NOT PROGRESSED TO THE MORE SERIOUS CONDITIONS OF APLASTIC ANEMIA OR AGRANULOCYTOSIS.
BECAUSE OF THE VERY LOW INCIDENCE OF AGRANULOCYTOSIS AND APLASTIC ANEMIA, THE VAST MAJORITY OF MINOR HEMATOLOGIC CHANGES OBSERVED IN MONITORING OF PATIENTS ON CARBAMAZEPINE ARE UNLIKELY TO SIGNAL THE OCCURRENCE OF EITHER ABNORMALITY. NONETHELESS, COMPLETE PRETREATMENT HEMATOLOGICAL TESTING SHOULD BE OBTAINED AS A BASELINE. IF A PATIENT IN THE COURSE OF TREATMENT EXHIBITS LOW OR DECREASED WHITE BLOOD CELL OR PLATELET COUNTS, THE PATIENT SHOULD BE MONITORED CLOSELY. DISCONTINUATION OF THE DRUG SHOULD BE CONSIDERED IF ANY EVIDENCE OF SIGNIFICANT BONE MARROW DEPRESSION DEVELOPS.

Before prescribing Carbatrol, the physician should be thoroughly familiar with the details of this prescribing information, particularly regarding use with other drugs, especially those which accentuate toxicity potential.

DESCRIPTION

CARBATROL* is an anticonvulsant and specific analgesic for trigeminal neuralgia, available for oral administration as 100 mg, 200 mg and 300 mg extended-release capsules of Carbamazepine, USP. Carbamazepine is a white to off-white powder, practically insoluble in water and soluble in alcohol and in acetone. Its molecular weight is 236.27. Its chemical name is 5H-dibenz[b,f]azepine-5-carboxamide, and its structural formula is:

Carbatrol is a multi-component capsule formulation consisting of three different types of beads: immediate-release beads, extended-release beads, and enteric-release beads. The three bead types are combined in a specific ratio to provide twice daily dosing of Carbatrol.

Inactive ingredients: citric acid, colloidal silicon dioxide, lactose monohydrate, microcrystalline cellulose, polyethylene glycol, povidone, sodium lauryl sulfate, talc, triethyl citrate and other ingredients.

CLINICAL PHARMACOLOGY

In controlled clinical trials, carbamazepine has been shown to be effective in the treatment of psychomotor and grand mal seizures, as well as trigeminal neuralgia.

Mechanism of Action

Carbamazepine has demonstrated anticonvulsant properties in rats and mice with electrically and chemically induced seizures. It appears to act by reducing polysynaptic responses and blocking the post-tetanic potentiation. Carbamazepine greatly reduces or abolishes pain induced by stimulation of the infraorbital nerve in cats and rats. It depresses thalamic potential and bulbar and polysynaptic reflexes, including the linguomandibular reflex in cats. Carbamazepine is chemically unrelated to other anticonvulsants or other drugs used to control the pain of trigeminal neuralgia. The mechanism of action remains unknown.

The principal metabolite of carbamazepine, carbamazepine-10,11-epoxide, has anticonvulsant activity as demonstrated in several in vivo animal models of seizures. Though clinical activity for the epoxide has been postulated, the significance of its activity with respect to the safety and efficacy of carbamazepine has not been established.

Pharmacokinetics

Carbamazepine (CBZ): Taken every 12 hours, carbamazepine extended-release capsules provide steady state plasma levels comparable to immediate-release carbamazepine tablets given every 6 hours, when administered at the same total mg daily dose.

Following a single 200 mg oral extended-release dose of carbamazepine, peak plasma concentration was 1.9 ± 0.3μg/mL and the time to reach the peak was 19 ± 7 hours. Following chronic administration (800 mg every 12 hours), the peak levels were 11.0 ± 2.5 μg/mL and the time to reach the peak was 5.9 ± 1.8 hours. The pharmacokinetics of extended-release carbamazepine is linear over the single dose range of 200-800 mg.

Carbamazepine is 76% bound to plasma proteins. Carbamazepine is primarily metabolized in the liver. Cytochrome P450 3A4 was identified as the major isoform responsible for the formation of carbamazepine-10,11-epoxide. Since carbamazepine induces its own metabolism, the half-life is also variable. Following a single extended-release dose of carbamazepine, the average half-life range from 35-40 hours and 12-17 hours on repeated dosing. The apparent oral clearance following a single dose was 25 ± 5 mL/min and following multiple dosing was 80 ± 30 mL/min.

After oral administration of^14C-carbamazepine, 72% of the administered radioactivity was found in the urine and 28% in the feces. This urinary radioactivity was composed largely of hydroxylated and conjugated metabolites, with only 3% of unchanged carbamazepine.

Carbamazepine-10,11-epoxide (CBZ-E): Carbamazepine-10,11-epoxide is considered to be an active metabolite of carbamazepine. Following a single 200 mg oral extended-release dose of carbamazepine, the peak plasma concentration of carbamazepine-10,11-epoxide was 0.11± 0.012 μg/mL and the time to reach the peak was 36 ± 6 hours. Following chronic administration of a extended-release dose of carbamazepine (800 mg every 12 hours), the peak levels of carbamazepine-10,11-epoxide were 2.2± 0.9 μg/mL and the time to reach the peak was 14 ± 8 hours. The plasma half-life of carbamazepine-10,11-epoxide following administration of carbamazepine is 34 ± 9 hours. Following a single oral dose of extended-release carbamazepine (200-800 mg) the AUC and Cmax of carbamazepine-10,11-epoxide were less than 10% of carbamazepine. Following multiple dosing of extended-release carbamazepine (800-1600 mg daily for 14 days), the AUC and Cmax of carbamazepine-10,11-epoxide were dose related, ranging from 15.7 μg.hr/mL and 1.5μg/mL at 800 mg/day to 32.6 μg.hr/mL and 3.2μg/mL at 1600 mg/day, respectively, and were less than 30% of carbamazepine. Carbamazepine-10,11-epoxide is 50% bound to plasma proteins.

Food Effect: A high fat meal diet increased the rate of absorption of a single 400 mg dose (mean Tmax was reduced from 24 hours, in the fasting state, to 14 hours and Cmax increased from 3.2 to 4.3 μg/mL) but not the extent (AUC) of absorption. The elimination half-life remains unchanged between fed and fasting state. The multiple dose study conducted in the fed state showed that the steady-state Cmax values were within the therapeutic concentration range. The pharmacokinetic profile of extended-release carbamazepine was similar when given by sprinkling the beads over applesauce compared to the intact capsule administered in the fasted state.

Special Populations

Hepatic Dysfunction: The effect of hepatic impairment on the pharmacokinetics of carbamazepine is not known. However, given that carbamazepine is primarily metabolized in the liver, it is prudent to proceed with caution in patients with hepatic dysfunction.

Renal Dysfunction: The effect of renal impairment on the pharmacokinetics of carbamazepine is not known.

Gender: No difference in the mean AUC and Cmax of carbamazepine and carbamazepine-10,11-epoxide was found between males and females.

Age: Carbamazepine is more rapidly metabolized to carbamazepine-10,11-epoxide in young children than adults. In children below the age of 15, there is an inverse relationship between CBZ-E/CBZ ratio and increasing age.

Race: No information is available on the effect of race on the pharmacokinetics of carbamazepine.

INDICATIONS AND USAGE

Epilepsy

Carbatrol is indicated for use as an anticonvulsant drug. Evidence supporting efficacy of carbamazepine as an anticonvulsant was derived from active drug-controlled studies that enrolled patients with the following seizure types:

1. Partial seizures with complex symptomatology (psychomotor, temporal lobe). Patients with these seizures appear to show greater improvements than those with other types.
2. Generalized tonic-clonic seizures (grand mal).
3. Mixed seizure patterns which include the above, or other partial or generalized seizures. Absence seizures (petit mal) do not appear to be controlled by carbamazepine (see PRECAUTIONS, General).

Trigeminal Neuralgia

Carbatrol is indicated in the treatment of the pain associated with true trigeminal neuralgia. Beneficial results have also been reported in glossopharyngeal neuralgia. This drug is not a simple analgesic and should not be used for the relief of trivial aches or pains.

CONTRAINDICATIONS

Carbamazepine should not be used in patients with a history of previous bone marrow depression, hypersensitivity to the drug, or known sensitivity to any of the tricyclic compounds, such as amitriptyline, desipramine, imipramine, protriptyline and nortriptyline. Likewise, on theoretical grounds its use with monoamine oxidase inhibitors is not recommended. Before administration of carbamazepine, MAO inhibitors should be discontinued for a minimum of 14 days, or longer if the clinical situation permits.

WARNINGS

Patients should be made aware that Carbatrol contains carbamazepine and should not be used in combination with any other medications containing carbamazepine.

Usage in Pregnancy

Carbamazepine can cause fetal harm when administered to a pregnant woman.

Epidemiological data suggest that there may be an association between the use of carbamazepine during pregnancy and congenital malformations, including spina bifida. The prescribing physician will wish to weigh the benefits of therapy against the risks in treating or counseling women of childbearing potential. If this drug is used during pregnancy, or if the patient becomes pregnant while taking this drug, the patient should be apprised of the potential hazard to the fetus.

Retrospective case reviews suggest that, compared with monotherapy, there may be a higher prevalence of teratogenic effects associated with the use of anticonvulsants in combination therapy.

In humans, transplacental passage of carbamazepine is rapid (30-60 minutes), and the drug is accumulated in the fetal tissues, with higher levels found in liver and kidney than in brain and lung.

Carbamazepine has been shown to have adverse effects in reproduction studies in rats when given orally in dosages 10-25 times the maximum human daily dosage (MHDD) of 1200 mg on a mg/kg basis or 1.5-4 times the MHDD on a mg/m2 basis. In rat teratology studies, 2 of 135 offspring showed kinked ribs at 250 mg/kg and 4 of 119 offspring at 650 mg/kg showed other anomalies (cleft palate, 1; talipes, 1; anophthalmos, 2). In reproduction studies in rats, nursing offspring demonstrated a lack of weight gain and an unkempt appearance at a maternal dosage level of 200 mg/kg.

Antiepileptic drugs should not be discontinued abruptly in patients in whom the drug is administered to prevent major seizures because of the strong possibility of precipitating status epilepticus with attendant hypoxia and threat to life. In individual cases where the severity and frequency of the seizure disorder are such that removal of medication does not pose a serious threat to the patient, discontinuation of the drug may be considered prior to and during pregnancy, although it cannot be said with any confidence that even minor seizures do not pose some hazard to the developing embryo or fetus.

Tests to detect defects using current accepted procedures should be considered a part of routine prenatal care in childbearing women receiving carbamazepine.

General

Patients with a history of adverse hematologic reaction to any drug may be particularly at risk.

Severe dermatologic reactions, including toxic epidermal necrolysis (Lyell’s syndrome) and Stevens-Johnson syndrome have been reported with carbamazepine. These reactions have been extremely rare. However, a few fatalities have been reported.

In patients with seizure disorder, carbamazepine should not be discontinued abruptly because of the strong possibility of precipitating status epilepticus with attendant hypoxia and threat to life.

Carbamazepine has shown mild anticholinergic activity; therefore, patients with increased intraocular pressure should be closely observed during therapy.

Because of the relationship of the drug to other tricyclic compounds, the possibility of activation of a latent psychosis and, in elderly patients, of confusion or agitation should be considered.

Co-administration of carbamazepine and delavirdine may lead to loss of virologic response and possible resistance to PRESCRIPTOR or to the class of non-nucleoside reverse transcriptase inhibitors.

PRECAUTIONS

General

Before initiating therapy, a detailed history and physical examination should be made.

Carbamazepine should be used with caution in patients with a mixed seizure disorder that includes atypical absence seizures, since in these patients carbamazepine has been associated with increased frequency of generalized convulsions (see INDICATIONS AND USAGE).

Therapy should be prescribed only after critical benefit-to-risk appraisal in patients with a history of cardiac, hepatic, or renal damage; adverse hematologic reaction to other drugs; or interrupted courses of therapy with carbamazepine.

Information for Patients

Patients should be made aware of the early toxic signs and symptoms of a potential hematologic problem, such as fever, sore throat, rash, ulcers in the mouth, easy bruising, petechial or purpuric hemorrhage, and should be advised to report to the physician immediately if any such signs or symptoms appear.

Since dizziness and drowsiness may occur, patients should be cautioned about the hazards of operating machinery or automobiles or engaging in other potentially dangerous tasks.

If necessary, the Carbatrol capsules can be opened and the contents sprinkled over food, such as a teaspoon of applesauce or other similar food products. Carbatrol capsules or their contents should not be crushed or chewed.

Carbatrol may interact with some drugs. Therefore, patients should be advised to report to their doctors the use of any other prescription or non-prescription medication or herbal products.

Laboratory Tests

Complete pretreatment blood counts, including platelets and possibly reticulocytes and serum iron, should be obtained as a baseline. If a patient in the course of treatment exhibits low or decreased white blood cell or platelet counts, the patient should be monitored closely. Discontinuation of the drug should be considered if any evidence of significant bone marrow depression develops.

Baseline and periodic evaluations of liver function, particularly in patients with a history of liver disease, must be performed during treatment with this drug since liver damage may occur. The drug should be discontinued immediately in cases of aggravated liver dysfunction or active liver disease.

Baseline and periodic eye examinations, including slit-lamp, funduscopy, and tonometry, are recommended since many phenothiazines and related drugs have been shown to cause eye changes.

Baseline and periodic complete urinalysis and BUN determinations are recommended for patients treated with this agent because of observed renal dysfunction.

Increases in total cholesterol, LDL and HDL have been observed in some patients taking anticonvulsants. Therefore, periodic evaluation of these parameters is also recommended.

Monitoring of blood levels (see CLINICAL PHARMACOLOGY) has increased the efficacy and safety of anticonvulsants. This monitoring may be particularly useful in cases of dramatic increase in seizure frequency and for verification of compliance. In addition, measurement of drug serum levels may aid in determining the cause of toxicity when more than one medication is being used.

Thyroid function tests have been reported to show decreased values with carbamazepine administered alone.

Hyponatremia has been reported in association with carbamazepine use, either alone or in combination with other drugs.

Interference with some pregnancy tests has been reported.

Drug Interactions

Clinically meaningful drug interactions have occurred with concomitant medications and include, but are not limited to the following:

Agents Highly Bound to Plasma Protein:

Carbamazepine is not highly bound to plasma proteins; therefore, administration of Carbatrol® to a patient taking another drug that is highly protein bound should not cause increased free concentrations of the other drug.

Agents that Inhibits Cytochrome P450 Isoenzymes and/or Epoxide Hydrolase:

Carbamazepine is metabolized mainly by cytochrome P450 (CYP) 3A4 to the active carbamazepine 10,11-epoxide, which is further metabolized to the trans-diol by epoxide hydrolase. Therefore, the potential exists for interaction between carbamazepine and any agent that inhibits CYP3A4 and/or epoxide hydrolase. Agents that are CYP3A4 inhibitors that have been found, or are expected, to increase plasma levels of Carbatrol® are the following:

Acetazolamide, azole antifungals, cimetidine, clarithromycin(1), dalfopristin, danazol, delavirdine, diltiazem, erythromycin(1), fluoxetine, fluvoxamine, grapefruit juice, isoniazid, itraconazole, ketoconazole, loratadine, nefazadone, niacinamide, nicotinamide, protease inhibitors, propoxyphene, quinine, quinupristin, troleandomycin, valproate(1), verapamil, zileuton.

(1)also inhibits epoxide hydrolase resulting in increased levels of the active metabolite carbamazepine 10, 11- epoxide

Thus, if a patient has been titrated to a stable dosage of Carbatrol®, and then begins a course of treatment with one of these CYP3A4 or epoxide hydrolase inhibitors, it is reasonable to expect that a dose reduction for Carbatrol® may be necessary.

Agents that Induce Cytochrome P450 Isoenzymes:

Carbamazepine is metabolized by CYP3A4. Therefore, the potential exists for interaction between carbamazepine and any agent that induces CYP3A4. Agents that are CYP inducers that have been found, or are expected, to decrease plasma levels of Carbatrol® are the following:

Cisplatin, doxorubicin HCL, felbamate, rifampin, phenobarbital, phenytoin(2), primidone, methsuximide, and theophylline

(2)Phenytoin plasma levels have also been reported to increase and decrease in the presence of carbamazepine, see below.

Thus, if a patient has been titrated to a stable dosage on Carbatrol®, and then begins a course of treatment with one of these CYP3A4 inducers, it is reasonable to expect that a dose increase for Carbatrol® may be necessary.

Agents with Decreased Levels in the Presence of Carbamazepine due to Induction of Cytochrome P450 Enzymes:

Carbamazepine is known to induce CYP1A2 and CYP3A4. Therefore, the potential exists for interaction between carbamazepine and any agent metabolized by one (or more) of these enzymes. Agents that have been found, or are expected to have decreased plasma levels in the presence of Carbatrol® due to induction of CYP enzymes are the following:

Acetaminophen, alprazolam, amitriptyline, bupropion, buspirone, citalopram, clobazam, clonazepam, clozapine, cyclosporin, delavirdine, desipramine, diazepam, dicumarol, doxycycline, ethosuximide, felbamate, felodipine, glucocorticoids, haloperidol, itraconazole, lamotrigine, levothyroxine, lorazepam, methadone, midazolam, mirtazapine, nortriptyline, olanzapine, oral contraceptives(3), oxcarbazepine, phenytoin(4), praziquantel, protease inhibitors, quetiapine, risperidone, theophylline, topiramate, tiagabine, tramadol, triazolam, trazodone(5), valproate, warfarin(6), ziprasidone, and zonisamide.

(3)Break through bleeding has been reported among patients receiving concomitant oral contraceptives and their reliability may be adversely affected.

(4)Phenytoin has also been reported to increase in the presence of carbamazepine. Careful monitoring of phenytoin plasma levels following co-medication with carbamazepine is advised.

(5)Following co-administration of carbamazepine 400mg/day with trazodone 100mg to 300mg daily, carbamazepine reduced trough plasma concentrations of trazodone (as well as meta-chlorophenylpiperazine [mCPP]) by 76 and 60% respectively, compared to precarbamazepine values.

(6)Warfarin’s anticoagulant effect can be reduced in the presence of carbamazepine.

Thus, if a patient has been titrated to a stable dosage on one of the agents in this category, and then begins a course of treatment with Carbatrol®, it is reasonable to expect that a dose increase for the concomitant agent may be necessary.

Agents with Increased Levels in the Presence of Carbamazepine:

Carbatrol® increases the plasma levels of the following agents:

Clomipramine HCl, phenytoin(7), and primidone

(7)Phenytoin has also been reported to decrease in the presence of carbamazepine. Careful monitoring of phenytoin plasma levels following co-medication with carbamazepine is advised.

Thus, if a patient has been titrated to a stable dosage on one of the agents in this category, and then begins a course of the treatment with Carbatrol®, it is reasonable to expect that a dose decrease for the concomitant agent may be necessary.

Pharmacological/Pharmacodynamic Interactions with Carbamazepine

Concomitant administration of carbamazepine and lithium may increase the risk of neurotoxic side effects.

Given the anticonvulsant properties of carbamazepine, Carbatrol® may reduce the thyroid function as has been reported with other anticonvulsants. Additionally, anti-malarial drugs, such as chloroquine and mefloquine, may antagonize the activity of carbamazepine.

Thus if a patient has been titrated to a stable dosage on one of the agents in this category, and then begins a course of treatment with Carbatrol®, it is reasonable to expect that a dose adjustment may be necessary.

Because of its primary CNS effect, caution should be used when Carbatrol® is taken with other centrally acting drugs and alcohol.

Carcinogenesis, Mutagenesis, Impairment of Fertility

Administration of carbamazepine to Sprague-Dawley rats for two years in the diet at doses of 25, 75, and 250 mg/kg/day (low dose approximately 0.2 times the maximum human daily dose of 1200 mg on a mg/m^2 basis), resulted in a dose-related increase in the incidence of hepatocellular tumors in females and of benign interstitial cell adenomas in the testes of males.

Carbamazepine must, therefore, be considered to be carcinogenic in Sprague-Dawley rats. Bacterial and mammalian mutagenicity studies using carbamazepine produced negative results. The significance of these findings relative to the use of carbamazepine in humans is, at present, unknown.

Usage in Pregnancy

Pregnancy Category D (See WARNINGS)

Labor and Delivery

The effect of carbamazepine on human labor and delivery is unknown.

Nursing Mothers

Carbamazepine and its epoxide metabolite are transferred to breast milk and during lactation. The concentrations of carbamazepine and its epoxide metabolite are approximately 50% of the maternal plasma concentration. Because of the potential for serious adverse reactions in nursing infants from carbamazepine, a decision should be made whether to discontinue nursing or to discontinue the drug, taking into account the importance of the drug to the mother.

Pediatric Use

Substantial evidence of carbamazepine effectiveness for use in the management of children with epilepsy (see INDICATIONS for specific seizure types) is derived from clinical investigations performed in adults and from studies in several in vitro systems which support the conclusion that (1) the pathogenic mechanisms underlying seizure propagation are essentially identical in adults and children, and (2) the mechanism of action of carbamazepine in treating seizures is essentially identical in adults and children.

Taken as a whole, this information supports a conclusion that the generally acceptable therapeutic range of total carbamazepine in plasma (i.e., 4-12 μg/mL) is the same in children and adults.

The evidence assembled was primarily obtained from short-term use of carbamazepine. The safety of carbamazepine in children has been systematically studied up to 6 months. No longer term data from clinical trials is available.

Geriatric Use

No systematic studies in geriatric patients have been conducted.

ADVERSE REACTIONS

General: If adverse reactions are of such severity that the drug must be discontinued, the physician must be aware that abrupt discontinuation of any anticonvulsant drug in a responsive patient with epilepsy may lead to seizures or even status epilepticus with its life-threatening hazards.

The most severe adverse reactions previously observed with carbamazepine were reported in the hemopoietic system (see BOX WARNING), the skin, and the cardiovascular system.

The most frequently observed adverse reactions, particularly during the initial phases of therapy, are dizziness, drowsiness, unsteadiness, nausea, and vomiting. To minimize the possibility of such reactions, therapy should be initiated at the lowest dosage recommended.

The following additional adverse reactions were previously reported with carbamazepine:

Hemopoietic System: Aplastic anemia, agranulocytosis, pancytopenia, bone marrow depression, thrombocytopenia, leukopenia, leukocytosis, eosinophilia, acute intermittent porphyria.

Skin: Pruritic and erythematous rashes, urticaria, toxic epidermal necrolysis (Lyell’s syndrome) (see WARNINGS), Stevens-Johnson syndrome (see WARNINGS), photosensitivity reactions, alterations in skin pigmentation, exfoliative dermatitis, erythema multiforme and nodosum, purpura, aggravation of disseminated lupus erythematosus, alopecia, and diaphoresis. In certain cases, discontinuation of therapy may be necessary. Isolated cases of hirsutism have been reported, but a causal relationship is not clear.

Cardiovascular System: Congestive heart failure, edema, aggravation of hypertension, hypotension, syncope and collapse, aggravation of coronary artery disease, arrhythmias and AV block, thrombophlebitis, thromboembolism, and adenopathy or lymphadenopathy. Some of these cardiovascular complications have resulted in fatalities. Myocardial infarction has been associated with other tricyclic compounds.

Liver: Abnormalities in liver function tests, cholestatic and hepatocellular jaundice, hepatitis.

Respiratory System: Pulmonary hypersensitivity characterized by fever, dyspnea, pneumonitis, or pneumonia.

Genitourinary System: Urinary frequency, acute urinary retention, oliguria with elevated blood pressure, azotemia, renal failure, and impotence. Albuminuria, glycosuria, elevated BUN, and microscopic deposits in the urine have also been reported.

Testicular atrophy occurred in rats receiving carbamazepine orally from 4-52 weeks at dosage levels of 50-400 mg/kg/day. Additionally, rats receiving carbamazepine in the diet for 2 years at dosage levels of 25, 75, and 250 mg/kg/day had a dose-related incidence of testicular atrophy and aspermatogenesis. In dogs, it produced a brownish discoloration, presumably a metabolite, in the urinary bladder at dosage levels of 50 mg/kg/day and higher. Relevance of these findings to humans is unknown.

Nervous System: Dizziness, drowsiness, disturbances of coordination, confusion, headache, fatigue, blurred vision, visual hallucinations, transient diplopia, oculomotor disturbances, nystagmus, speech disturbances, abnormal involuntary movements, peripheral neuritis and paresthesias, depression with agitation, talkativeness, tinnitus, and hyperacusis.

There have been reports of associated paralysis and other symptoms of cerebral arterial insufficiency, but the exact relationship of these reactions to the drug has not been established.

Isolated cases of neuroleptic malignant syndrome have been reported with concomitant use of psychotropic drugs.

Digestive System: Nausea, vomiting, gastric distress and abdominal pain, diarrhea, constipation, anorexia, and dryness of the mouth and pharynx, including glossitis and stomatitis.

Eyes: Scattered punctate cortical lens opacities, as well as conjunctivitis, have been reported. Although a direct causal relationship has not been established, many phenothiazines and related drugs have been shown to cause eye changes.

Musculoskeletal System: Aching joints and muscles, and leg cramps.

Metabolism: Fever and chills, inappropriate antidiuretic hormone (ADH) secretion syndrome has been reported. Cases of frank water intoxication, with decreased serum sodium (hyponatremia) and confusion have been reported in association with carbamazepine use (see PRECAUTIONS, Laboratory Tests). Decreased levels of plasma calcium have been reported.

Other: Isolated cases of a lupus erythematosus-like syndrome have been reported. There have been occasional reports of elevated levels of cholesterol, HDL cholesterol, and triglycerides in patients taking anticonvulsants.

A case of aseptic meningitis, accompanied by myoclonus and peripheral eosinophilia, has been reported in a patient taking carbamazepine in combination with other medications. The patient was successfully dechallenged, and the meningitis reappeared upon rechallenge with carbamazepine.

DRUG ABUSE AND DEPENDENCE

No evidence of abuse potential has been associated with carbamazepine, nor is there evidence of psychological or physical dependence in humans.

OVERDOSAGE

Acute Toxicity

Lowest known lethal dose: adults, >60 g (39-year-old man). Highest known doses survived: adults, 30 g (31-year-old woman); children, 10 g (6-year-old boy); small children, 5 g (3-year-old girl).

Oral LD50 in animals (mg/kg): mice, 1100-3750; rats, 3850-4025; rabbits, 1500-2680; guinea pigs, 920.

Signs and Symptoms

The first signs and symptoms appear after 1-3 hours. Neuromuscular disturbances are the most prominent. Cardiovascular disorders are generally milder, and severe cardiac complications occur only when very high doses (>60 g) have been ingested.

Respiration: Irregular breathing, respiratory depression.

Cardiovascular System: Tachycardia, hypotension or hypertension, shock, conduction disorders.

Nervous System and Muscles: Impairment of consciousness ranging in severity to deep coma.
Convulsions, especially in small children. Motor restlessness, muscular twitching, tremor, athetoid movements, opisthotonos, ataxia, drowsiness, dizziness, mydriasis, nystagmus, adiadochokinesia, ballism, psychomotor disturbances, dysmetria. Initial hyperreflexia, followed by hyporeflexia.

Gastrointestinal Tract: Nausea, vomiting.

Kidneys and Bladder: Anuria or oliguria, urinary retention

Laboratory Findings: Isolated instances of overdosage have included leukocytosis, reduced leukocyte count, glycosuria, and acetonuria. ECG may show dysrhythmias.

Combined Poisoning: When alcohol, tricyclic antidepressants, barbiturates, or hydantoins are taken at the same time, the signs and symptoms of acute poisoning with carbamazepine may be aggravated or modified.

Treatment

For the most up to date information on management of carbamazepine overdose, please contact the poison center for your area by calling 1-800-222-1222. The prognosis in cases of carbamazepine poisoning is generally favorable. Of 5,645 cases of carbamazepine exposures reported to US poison centers in 2002, a total of 8 deaths (0.14% mortality rate) occurred. Over 39% of the cases reported to these poison centers were managed safely at home with conservative care. Successful management of large or intentional carbamazepine exposures requires implementation of supportive care, frequent monitoring of serum drug concentrations, as well as aggressive but appropriate gastric decontamination.

Elimination of the Drug: The primary method for gastric decontamination of carbamazepine overdose is use of activated charcoal. For substantial recent ingestions, gastric lavage may also be considered. Administration of activated charcoal prior to hospital assessment has the potential to significantly reduce drug absorption. There is no specific antidote. In overdose, absorption of carbamazepine may be prolonged and delayed. More than one dose of activated charcoal may be beneficial in patients that have evidence of continued absorption (e.g., rising serum carbamazepine levels).

Measures to Accelerate Elimination:
The data on use of dialysis to enhance elimination in carbamazepine is scarce. Dialysis, particularly high flux or high efficiency hemodialysis, may be considered in patients with severe carbamazepine poisoning associated with renal failure or in cases of status epilepticus, or where there are rising serum drug levels and worsening clinical status despite appropriate supportive care and gastric decontamination. For severe cases of carbamazepine overdose unresponsive to other measures, charcoal hemoperfusion may be used to enhance drug clearance.

Respiratory Depression: Keep the airways free; resort, if necessary, to endotracheal intubation, artificial respiration, and administration of oxygen.

Hypotension, Shock: Keep the patient’s legs raised and administer a plasma expander. If blood pressure fails to rise despite measures taken to increase plasma volume, use of vasoactive substances should be considered.

Convulsions: Diazepam or barbiturates.

Warning: Diazepam or barbiturates may aggravate respiratory depression (especially in children), hypotension, and coma. However, barbiturates should not be used if drugs that inhibit monoamine oxidase have also been taken by the patient either in overdosage or in recent therapy (within 1 week).

Surveillance:Respiration, cardiac function (ECG monitoring), blood pressure, body temperature, pupillary reflexes, and kidney and bladder function should be monitored for several days.

Treatment of Blood Count Abnormalities: If evidence of significant bone marrow depression develops, the following recommendations are suggested: (1) stop the drug, (2) perform daily CBC, platelet, and reticulocyte counts, (3) do a bone marrow aspiration and trephine biopsy immediately and repeat with sufficient frequency to monitor recovery.

Special periodic studies might be helpful as follows: (1) white cell and platelet antibodies, (2)^59Fe-ferrokinetic studies, (3) peripheral blood cell typing, (4) cytogenetic studies on marrow and peripheral blood, (5) bone marrow culture studies for colony-forming units, (6) hemoglobin electrophoresis for A2 and F hemoglobin, and (7) serum folic acid and B12 levels.

A fully developed aplastic anemia will require appropriate, intensive monitoring and therapy, for which specialized consultation should be sought.

DOSAGE AND ADMINISTRATION

Monitoring of blood levels has increased the efficacy and safety of anticonvulsants (see PRECAUTIONS, Laboratory Tests). Dosage should be adjusted to the needs of the individual patients. A low initial daily dosage with gradual increase is advised. As soon as adequate control is achieved, the dosage may be reduced very gradually to the minimum effective level. The Carbatrol capsules may be opened and the beads sprinkled over food, such as a teaspoon of applesauce or other similar food products if this method of administration is preferred. Carbatrol capsules or their contents should not be crushed or chewed. Carbatrol can be taken with or without meals.

Carbatrol is an extended-release formulation for twice a day administration. When converting patients from immediate release carbamazepine to Carbatrol extended-release capsules, the same total daily mg dose of carbamazepine should be administered.

Epilepsy (see INDICATIONS AND USAGE)

Adults and children over 12 years of age. Initial: 200 mg twice daily. Increase at weekly intervals by adding up to 200 mg/day until the optimal response is obtained. Dosage generally should not exceed 1000 mg per day in children 12-15 years of age, and 1200 mg daily in patients above 15 years of age. Doses up to 1600 mg daily have been used in adults. Maintenance: Adjust dosage to the minimum effective level, usually 800-1200 mg daily.

Children under 12 years of age: Children taking total daily dosages of immediate-release carbamazepine of 400 mg or greater may be converted to the same total daily dosage of Carbatrol extended-release capsules, using a twice daily regimen. Ordinarily, optimal clinical response is achieved at daily doses below 35 mg/kg. If satisfactory clinical response has not been achieved, plasma levels should be measured to determine whether or not they are in the therapeutic range. No recommendation regarding the safety of Carbatrol for use at doses above 35 mg/kg/24 hours can be made.

Combination Therapy: Carbatrol may be used alone or with other anticonvulsants. When added to existing anticonvulsant therapy, the drug should be added gradually while the other anticonvulsants are maintained or gradually decreased, except phenytoin, which may have to be increased (see PRECAUTIONS, Drug Interactions, and Pregnancy Category D).

Trigeminal Neuralgia (see INDICATIONS AND USAGE)

Initial: On the first day, start with one 200 mg capsule. This daily dose may be increased by up to 200 mg/day every 12 hours only as needed to achieve freedom from pain. Do not exceed 1200 mg daily.

Maintenance: Control of pain can be maintained in most patients with 400-800 mg daily. However, some patients may be maintained on as little as 200 mg daily, while others may require as much as 1200 mg daily. At least once every 3 months throughout the treatment period, attempts should be made to reduce the dose to the minimum effective level or even to discontinue the drug.

HOW SUPPLIED

Carbatrol (carbamazepine) extended-release capsules is supplied in three dosage strengths.

300 mg-Two-piece hard gelatin capsule (black opaque body with bluish green opaque cap) printed with the Shire logo in white ink.

Supplied in bottles of 120 ............................NDC 54868-5432-0

Store at 25°C (77°F); excursions permitted to 15-30°C (59-86°F) [see USP controlled room temperature]. PROTECT FROM LIGHT AND MOISTURE.

Manufactured for:

Shire US Inc.

725 Chesterbrook Blvd, Wayne PA 19087

1-800-828-2088, Made in U.S.A. © 2011 Shire US Inc.

001724 172 1207 013 (Rev 01/2011)

Registered in the US Patent and Trade Office

Relabeling and Repackaging by:
Physicians Total Care, Inc.
Tulsa, OK 74146

Medication Guide
CARBATROL (CAR-BA-TROL)
(carbamazepine)
Extended-Release Capsules

Read this Medication Guide before you start taking CARBATROL and each time you get a refill. There may be new information. This information does not take the place of talking to your healthcare provider about your medical condition or treatment.

What is the most important information I should know about CARBATROL?

Do not stop taking CARBATROL without first talking to your healthcare provider.

Stopping CARBATROL suddenly can cause serious problems.

CARBATROL can cause serious side effects, including:

1. CARBATROL may cause rare but serious rashes that may lead to death. These serious skin reactions are more likely to happen within the first four months of CARBATROL treatment but may occur at later times. These reactions can happen in anyone, but are more likely in people of Asian descent. If you are of Asian descent you may need a genetic blood test before you take CARBATROL to see if you are at a higher risk for serious skin reactions with this medicine. Symptoms may include:

- skin rash
- hives
- sores in your mouth
- blistering or peeling of the skin

2. CARBATROL may cause rare but serious blood problems. Symptoms may include:

- fever, sore throat or other infections that come and go or do not go away
- easy bruising
- red or purple spots on your body
- bleeding gums or nose bleeds
- severe fatigue or weakness

3. Like other antiepileptic drugs, CARBATROL may cause suicidal thoughts or actions in a very small number of people, about 1 in 500.

Call your healthcare provider right away if you have any of these symptoms, especially if they are new, worse, or worry you:

- thoughts about suicide or dying
- attempt to commit suicide
- new or worse depression
- new or worse anxiety
- feeling agitated or restless
- panic attacks
- trouble sleeping (insomnia)
- new or worse irritability
- acting aggressive, being angry, or violent
- acting on dangerous impulses
- an extreme increase in activity and talking (mania)
- other unusual changes in behavior or mood

How can I watch for early symptoms of suicidal thoughts and actions?

- Pay attention to any changes, especially sudden changes, in mood, behaviors, thoughts, or feelings.
- Keep all follow-up visits with your healthcare provider as scheduled.
- Call your healthcare provider between visits as needed, especially if you are worried about symptoms.

Do not stop CARBATROL without first talking to a healthcare provider.

Stopping CARBATROL suddenly can cause serious problems.

Suicidal thoughts or actions can be caused by things other than medicines. If you have suicidal thoughts or actions, your healthcare provider may check for other causes.

What is CARBATROL?

CARBATROL is a medicine used to treat:

- certain types of seizures (partial, tonic-clonic, mixed)
- certain types of nerve pain (trigeminal and glossopharyngeal neuralgia).

CARBATROL is not a regular pain medicine and should not be used for aches or pains.

Who should not take CARBATROL?

Do not take CARBATROL if you:

- have a history of bone marrow depression
- are allergic to carbamazepine or any of the ingredients in CARBATROL. See the end of this Medication Guide for a complete list of ingredients in CARBATROL.
- take nefazodone
- are allergic to antidepressant medications called tricyclic (TCAs).
- have taken a medicine called Monoamine Oxidase Inhibitor (MAOI) in the last 14 days.

Ask your healthcare provider or pharmacist for a list of these medicines if you are not sure.

What should I tell my healthcare provider before taking CARBATROL?

Before you take CARBATROL, tell your healthcare provider if you:

- have or ever had heart problems
- have or ever had blood problems
- have or ever had liver or kidney problems
- have or ever had allergic reactions to medicines
- have or ever had increased pressure in your eye
- have or have had suicidal thoughts or actions, depression or mood problems
- have any other medical conditions
- drink grapefruit juice or eat grapefruit
- use birth control. CARBATROL may make your birth control less effective. Tell your healthcare provider if your menstrual bleeding changes while you take birth control and CARBATROL.
- are pregnant or plan to become pregnant. CARBATROL may harm your unborn baby. Tell your healthcare provider right away if you become pregnant while taking CARBATROL. You and your healthcare provider should decide if you should take CARBATROL while you are pregnant.

- If you become pregnant while taking CARBATROL, talk to your healthcare provider about registering with the North American Antiepileptic Drug (NAAED) Pregnancy Registry. The purpose of this registry is to collect information about the safety of antiepileptic medicine during pregnancy. You can enroll in this registry by calling 1-888-233-2334.

- are breastfeeding or plan to breastfeed. CARBATROL passes into your breast milk. You and your healthcare provider should discuss whether you should take CARBATROL or breastfeed. You should not do both.

Tell your healthcare provider about all the medicines you take, including prescription and non-prescription medicines, vitamins, and herbal supplements.

Taking CARBATROL with certain other medicines can cause side effects or affect how well they work. Do not start or stop other medicines without talking to your healthcare provider.

Know the medicines you take. Keep a list of them and show it to your healthcare provider and pharmacist when you get a new medicine.

How should I take CARBATROL?

- Take CARBATROL exactly as prescribed. Your doctor will tell you how much CARBATROL to take.
- Your healthcare provider may change your dose. Do not change your dose of CARBATROL without talking to your healthcare provider.
- Do not stop taking CARBATROL without first talking to your healthcare provider. Stopping CARBATROL suddenly can cause serious problems. Stopping seizure medicine suddenly in a patient who has epilepsy can cause seizures that will not stop (status epilepticus).
- Take CARBATROL with or without food.
- Do not crush, chew, or break CARBATROL capsules or the beads inside of the capsules. But, CARBATROL capsules can be opened and sprinkled over food such as a teaspoon of applesauce. Tell your healthcare provider if you can not swallow CARBATROL whole.
- If you take too much CARBATROL, call your healthcare provider or local Poison Control Center right away.

What should I avoid while taking CARBATROL?

- Do not drink alcohol or take other drugs that may make you sleepy or dizzy while taking CARBATROL until you talk to your healthcare provider. CARBATROL taken with alcohol or drugs may make your sleepiness or dizziness worse.
- Do not drive, or operate heavy machinery, or do other dangerous activities until you know how CARBATROL affects you. CARBATROL can slow your thinking and motor skills.

What are the possible side effects of CARBATROL?

See "What is the most important information I should know about CARBATROL?"

CARBATROL may cause other serious side effects including:

Irregular heartbeat - symptoms include:

- Fast, slow, or pounding heartbeat
- Shortness of breath
- Feeling lightheaded
- Fainting

Liver problems - symptoms include:

- yellowing of your skin or the whites of your eyes
- dark urine
- pain on the right side of your stomach area (abdominal pain)
- easy bruising
- loss of appetite
- nausea or vomiting

Get medical help right away if you have any of the symptoms listed above or listed in "What is the most important information I should know about CARBATROL".

The most common side effects of CARBATROL include:

- dizziness
- drowsiness
- problems with walking and coordination (unsteadiness)
- nausea
- vomiting

These are not all the side effects of CARBATROL. For more information, ask your healthcare provider or pharmacist.

Tell your healthcare provider if you have any side effect that bothers you. or that does not go away.

Call your doctor for medical advice about side effects. You may report side effects to FDA at 1-800-FDA-1088.

How should I store CARBATROL?

- Store CARBATROL between 59°F to 86°F (15°C to 30°C).
- Keep CARBATROL out of the light.
- Keep CARBATROL capsules dry.

Keep CARBATROL and all medicines out of the reach of children.

General information about CARBATROL

Medicines are sometimes prescribed for purposes other than those listed in a Medication Guide. Do not use CARBATROL for a condition for which it was not prescribed. Do not give CARBATROL to other people, even if they have the same symptoms that you have. It may harm them.

This Medication Guide summarizes the most important information about CARBATROL. If you would like more information, talk with your healthcare provider. You can ask your pharmacist or healthcare provider for information about CARBATROL that is written for health professionals.

For more information go to www.carbatrol.com or call 1-800-828-2088.

What are the ingredients in CARBATROL?

Active ingredient: carbamazepine

Inactive ingredients: citric acid, colloidal silicon dioxide, lactose monohydrate, microcrystalline cellulose, polyethylene glycol, povidone, sodium lauryl sulfate, talc, triethyl citrate and Eudragit.

In addition:

- the 100 mg capsules contain gelatin-NF, FD&C Blue #2, Yellow Iron Oxide, and titanium dioxide and are imprinted with white ink
- the 200 mg capsules contain gelatin-NF, FD&C Red #3, FD&C Yellow #6, Yellow Iron Oxide, FD&C Blue #2, and titanium dioxide, and are imprinted with white ink
- the 300 mg capsules contain gelatin-NF, FD&C Blue #2, FD&C Yellow #6, Red Iron Oxide, Yellow Iron Oxide, and titanium dioxide, and are imprinted with white ink

This Medication Guide has been approved by the US Food and Drug Administration.

Shire US Inc.

Wayne, PA 19087

Issued [01/2011]

PRINCIPAL DISPLAY PANEL

CARBATROL (CAR-BA-TROL)

(carbamazepine)

300 mg